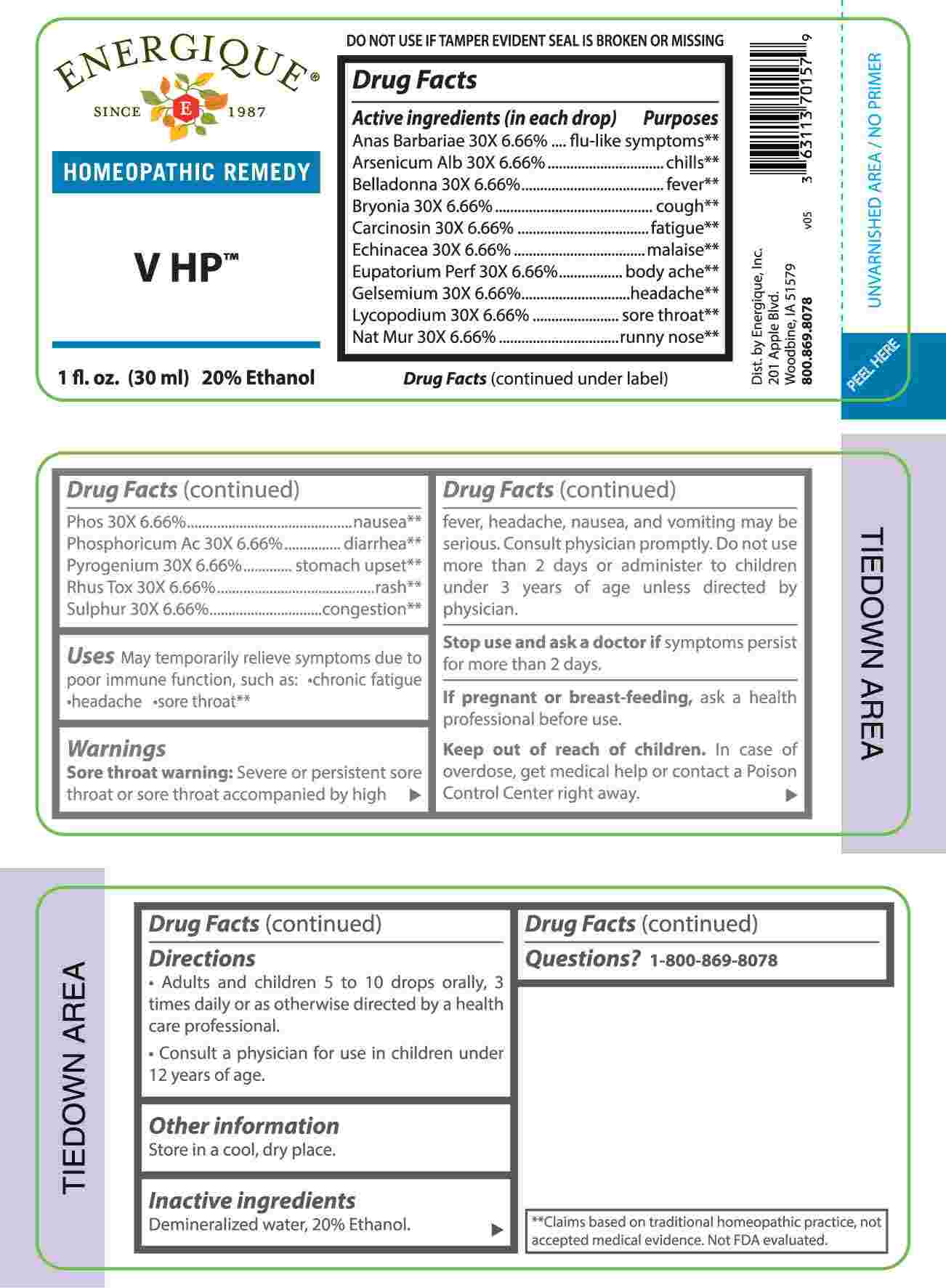 DRUG LABEL: V HP
NDC: 44911-0717 | Form: LIQUID
Manufacturer: Energique, Inc.
Category: homeopathic | Type: HUMAN OTC DRUG LABEL
Date: 20240813

ACTIVE INGREDIENTS: CAIRINA MOSCHATA HEART/LIVER AUTOLYSATE 30 [hp_X]/1 mL; ARSENIC TRIOXIDE 30 [hp_X]/1 mL; ATROPA BELLADONNA 30 [hp_X]/1 mL; BRYONIA ALBA ROOT 30 [hp_X]/1 mL; HUMAN BREAST TUMOR CELL 30 [hp_X]/1 mL; ECHINACEA ANGUSTIFOLIA WHOLE 30 [hp_X]/1 mL; EUPATORIUM PERFOLIATUM FLOWERING TOP 30 [hp_X]/1 mL; GELSEMIUM SEMPERVIRENS ROOT 30 [hp_X]/1 mL; LYCOPODIUM CLAVATUM SPORE 30 [hp_X]/1 mL; SODIUM CHLORIDE 30 [hp_X]/1 mL; PHOSPHORIC ACID 30 [hp_X]/1 mL; PHOSPHORUS 30 [hp_X]/1 mL; RANCID BEEF 30 [hp_X]/1 mL; TOXICODENDRON PUBESCENS LEAF 30 [hp_X]/1 mL; SULFUR 30 [hp_X]/1 mL
INACTIVE INGREDIENTS: WATER; ALCOHOL

DRUG FACTS:

ACTIVE INGREDIENTS:

(in each drop) Anas Barbariae 30X 6.66%, Arsenicum Album 30X 6.66%, Belladonna 30X 6.66%, Bryonia 30X 6.66%, Carcinosin 30X 6.66%, Echinacea 30X 6.66%, Eupatorium Perfoliatum 30X 6.66%, Gelsemium Sempervirens 30X 6.66%, Lycopodium Clavatum 30X 6.66%, Natrum Muriaticum 30X 6.66%, Phosphoricum Acidum 30X 6.66%, Phosphorus 30X 6.66%, Pyrogenium 30X 6.66%, Rhus Tox 30X 6.66%, Sulphur 30X 6.66%.

PURPOSE:

Anas Barbariae – flu-like symptoms,** Arsenicum Album - chills,** Belladonna - fever,** Bryonia - cough,** Carcinosin - fatigue,** Echinacea - malaise,** Eupatorium Perfoliatum – body ache,** Gelsemium Sempervirens - headache,** Lycopodium Clavatum – sore throat,** Natrum Muriaticum – runny nose,** Phosphorus - nausea,** Phosphoricum Acidum – diarrhea,** Pyrogenium – stomach upset,** Rhus Tox - rash,** Sulphur – congestion**

USES:

May temporarily relieve symptoms due to poor immune function, such:

• chronic fatigue • headache • sore throat**

**Claims based on traditional homeopathic practice, not accepted medical evidence. Not FDA evaluated.

WARNINGS:

Sore throat warning: Severe or persistent sore throat or sore throat accompanied by high fever, headache, nausea, and vomiting may be serious. Consult physician promptly. Do not use more than 2 days or administer to children under 3 years of age unless directed by a physician.

Stop use and ask a doctor if symptoms persist for more than 2 days.

If pregnant or breast-feeding, ask a health professional before use.

Keep out of reach of children. In case of overdose, get medical help or contact a Poison Control Center right away.

DO NOT USE IF TAMPER EVIDENT SEAL IS BROKEN OR MISSING

Store in a cool, dry place.

KEEP OUT OF REACH OF CHILDREN:

In case of overdose, get medical help or contact a Poison Control Center right away.

DIRECTIONS:

• Adults and children 5 to 10 drops orally, 3 times daily or as otherwise directed by a health care professional.

• Consult a physician for use in children under 12 years of age.

INACTIVE INGREDIENTS:

Demineralized water, 20% Ethanol.

QUESTIONS:

Dist. by Energique, Inc.
201 Apple Blvd.
Woodbine, IA 51579

800-869-8078

PACKAGE LABEL DISPLAY:

ENERGIQUE

SINCE 1987
HOMEOPATHIC REMEDY
V HP
1 fl. oz. (30 ml)